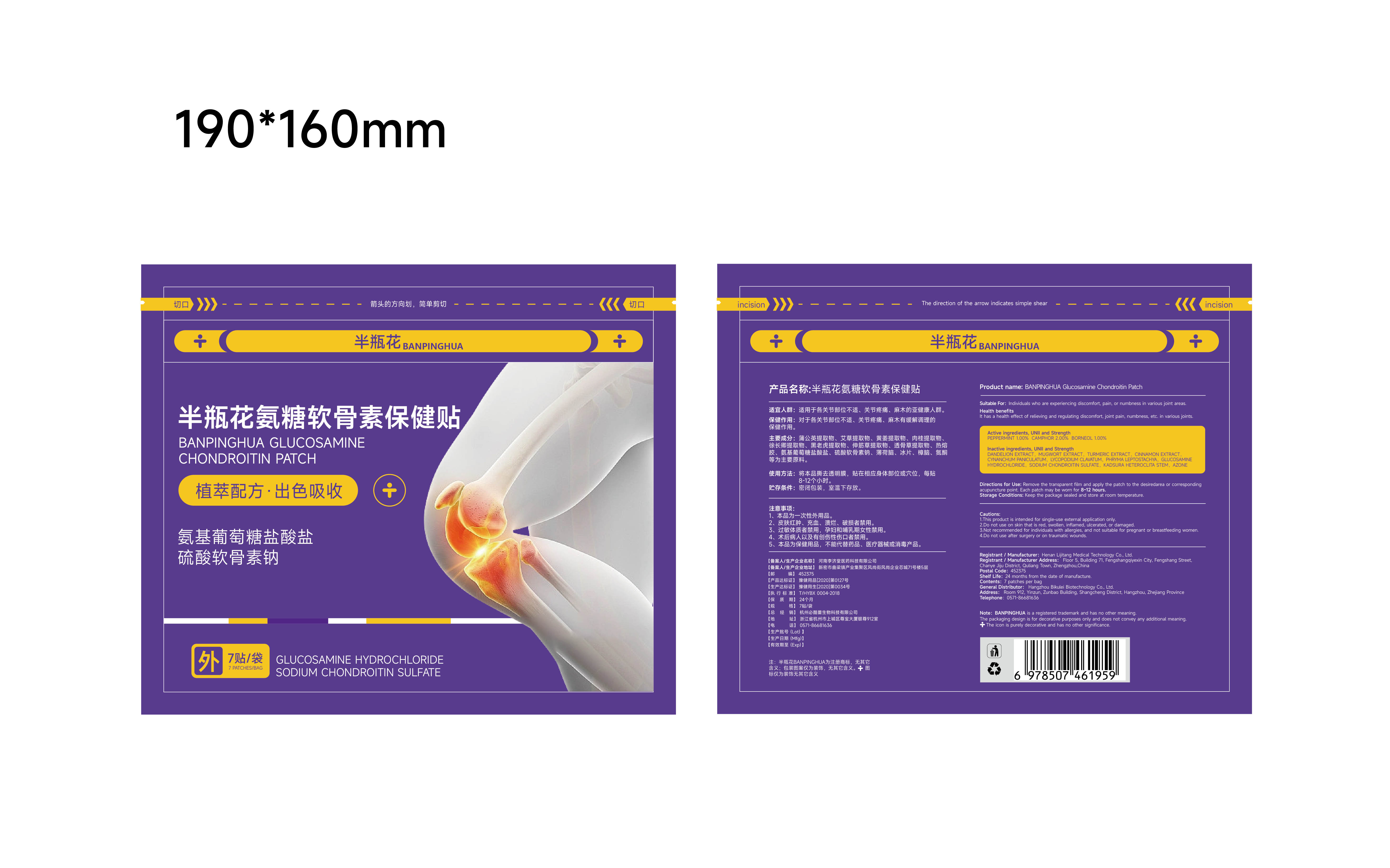 DRUG LABEL: BANPINGHUA Glucosamine Chondroitin Patch
NDC: 85305-004 | Form: PATCH
Manufacturer: Henan Lijitang Medical Technology Co., Ltd.
Category: otc | Type: HUMAN OTC DRUG LABEL
Date: 20251106

ACTIVE INGREDIENTS: BORNEOL 0.01 g/1 1; PEPPERMINT 0.01 g/1 1; CAMPHORIC ACID 0.02 g/1 1
INACTIVE INGREDIENTS: ARTEMISIA PRINCEPS LEAF; KADSURA COCCINEA ROOT; TARAXACUM OFFICINALE ROOT; GLUCOSAMINE HYDROCHLORIDE; CYNANCHUM PANICULATUM ROOT; CHINESE CINNAMON; LYCOPODIUM JAPONICUM TOP; SODIUM CHONDROITIN SULFATE (PORCINE; 5500 MW); TURMERIC; PHRYMA LEPTOSTACHYA WHOLE; LAUROCAPRAM

85305-004 BANPINGHUA Glucosamine Chondroitin Patch

ACTIVE INGREDIENT

PEPPERMINT 1%
CAMPHOR 2%
BORNEOL 1%

PURPOSE

Analgesia

INDICATIONS AND USAGE

Suitable For: Individuals who are experiencing discomfort, pain, or numbness in various joint areas.
It has a health effect of relieving and requlating discomfort, joint pain, numbness, etc. in various joints.

WARNINGS

This product is intended for single-use external application only.

DO NOT USE

2.Do not use on skin that is red, swollen, inflamed, ulcerated, or damaged.
3.Not recommended for individuals with allergies, and not suitable for pregnant or breastfeeding women.

WHEN USING

Suitable For: individuals who are experiencing discomfort, pain, or numbness in various joint areas.

KEEP OUT OF REACH OF CHILDREN SECTION

DOSAGE AND ADMINISTRATION

Directions for Use: Remove the transparent film and apply the patch to the desiredarea or corresponding acupuncture point. Each patch may be worn for 8-12 hours.

INACTIVE INGREDIENT

DANDELION EXTRACT, MUGWORT EXTRACT, TURMERIC EXTRACT, CINNAMON EXTRACTCYNANCHUM PANICULATUM. LYCOPODIUM CLAVATUM, PHRYMA LEPTOSTACHYA, GLUCOSAMINEHYDROCHLORIDE, SODIUM CHONDROITIN SULFATE, KADSURA HETEROCLITA STEM, AZONE